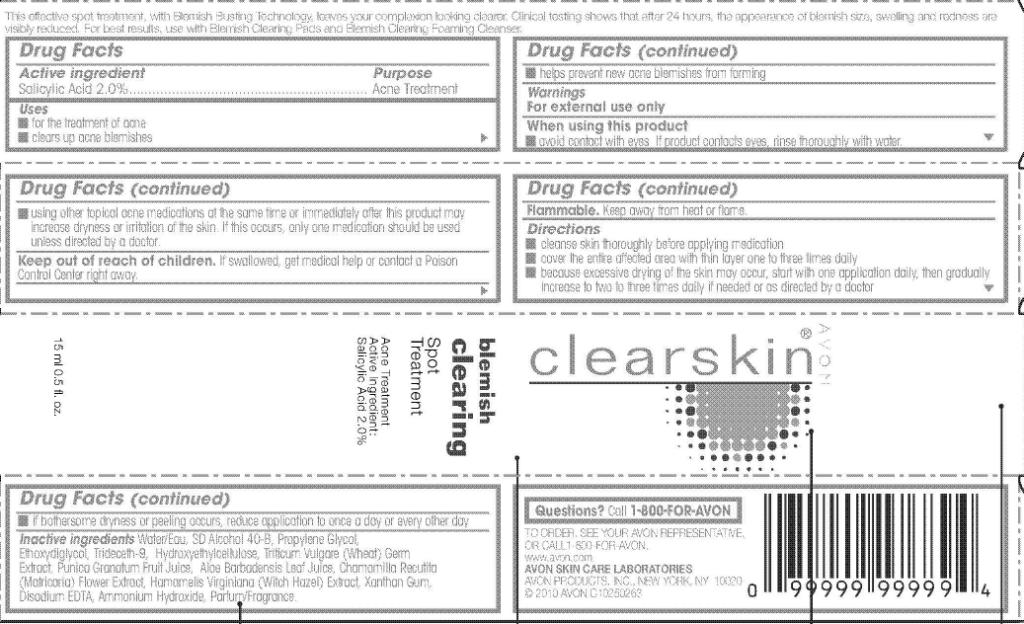 DRUG LABEL: Clearskin
NDC: 10096-0223 | Form: GEL
Manufacturer: Avon Products, Inc.
Category: otc | Type: HUMAN OTC DRUG LABEL
Date: 20100614

ACTIVE INGREDIENTS: Salicylic acid 0.3 mL/15 mL
INACTIVE INGREDIENTS: WATER; PROPYLENE GLYCOL

Drug Facts

Active ingredient Purpose
Salicylic Acid 2.0%.........................Acne Treatment

Uses

- for the treatment of acne
- clears up acne blemishes
- helps prevent new acne blemishes from forming

Warnings
For external use only

When using this product

- avoid contact with eyes. If product contacts eyes, rinse thoroughly with water.
- using other topical acne medications at the same time or immediately after this product may increase dryness or irritation of the skin. If this occurs, only one medication should be used unless directed by a doctor.

Keep out of reach of children. If swallowed, get medical
help or contact a Poison Control Center right away.

SAFE HANDLING WARNING

Flammable. Keep away from heat or flame.

Directions

- cleanse skin thoroughly before applying medication
- cover the entire affected area with thin layer one to three times daily
- because excessive drying of the skin may occur, start with one application daily, then gradually increase to two to three times daily if needed or as directed by a doctor
- if bothersome dryness, irritation or peeling occurs, reduce application to once a day or every other day

Inactive ingredients

WATER/EAU
SD ALCOHOL 40-B
PROPYLENE GLYCOL
ETHOXYDIGLYCOL
TRIDECETH-9
HYDROXYETHYLCELLULOSE
TRITICUM VULGARE (WHEAT) GERM EXTRACT
PUNICA GRANATUM FRUIT JUICE
ALOE BARBADENSIS LEAF JUICE
CHAMOMILLA RECUTITA (MATRICARIA) FLOWER EXTRACT
HAMAMELIS VIRGINIANA (WITCH HAZEL) EXTRACT
XANTHAN GUM
DISODIUM EDTA
AMMONIUM HYDROXIDE
PARFUM/FRAGRANCE

Questions? Call 1-800-FOR-AVON